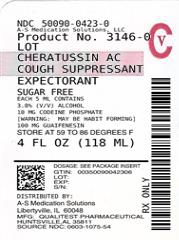 DRUG LABEL: Cheratussin AC
NDC: 50090-0423 | Form: LIQUID
Manufacturer: A-S Medication Solutions
Category: otc | Type: HUMAN OTC DRUG LABEL
Date: 20190124
DEA Schedule: CV

ACTIVE INGREDIENTS: CODEINE PHOSPHATE 10 mg/5 mL; GUAIFENESIN 100 mg/5 mL
INACTIVE INGREDIENTS: ALCOHOL; CARAMEL; ANHYDROUS CITRIC ACID; FD&C RED NO. 40; GLYCERIN; MENTHOL, UNSPECIFIED FORM; WATER; SACCHARIN SODIUM; SODIUM BENZOATE; SORBITOL

Active ingredients (in each 5 mL = 1 tsp)

Codeine phosphate, USP 10 mg

Guaifenesin, USP 100 mg

Purpose

Cough suppressant

Expectorant

Uses

- temporarily relieves cough due to minor throat and bronchial irritation as may occur with a cold
- helps loosen phlegm (mucus) and thin bronchial secretions to make coughs more productive
- calms the cough control center and relieves coughing

Do not use

- in a child under 2 years of age
- if you or your child has a chronic pulmonary disease or shortness of breath
- if your child is taking other drugs, unless directed by a doctor

Ask a doctor before use if you have

- cough that occurs with excessive phlegm (mucus)
- cough that lasts or is chronic such as occurs with smoking, asthma, chronic bronchitis, or emphysema

When using this product constipation may occur or be aggravated

Stop use and ask a doctor if cough lasts more than 7 days, comes back or is accompanied by fever, rash, or persistent headache. These could be signs of a serious condition.

PREGNANCY OR BREAST FEEDING

If pregnant or breast-feeding, ask a health professional before use.

Keep out of reach of children.

In case of overdose, get medical help or contact a Poison Control Center right away.

Directions

- take every 4 hours
- do not take more than 6 doses in any 24-hour period

adults and children 12 years and over | take 10 mL (2 tsp)
children 6 years to under 12 years | take 5 mL (1 tsp)
children 2 years to under 6 years | consult a doctor
children under 2 years | do not use

Attention: A special measuring device should be used to give an accurate dose of this product to children under 6 years of age. Giving a higher dose than recommended by a doctor could result in serious side effects for your child.

Other information

store at 15° to 30°C (59° to 86°F)

You may report serious side effects to: 130 Vintage Drive, Huntsville, AL 35811.

Inactive ingredients

alcohol, caramel, citric acid, FD&C red #40, flavor, glycerin, menthol racemic, purified water, saccharin sodium, sodium benzoate, sorbitol solution

Made in the USA
for Qualitest Pharmaceuticals
Huntsville, AL 35811

Rev. 1/15 R7 8081202 1075

HOW SUPPLIED

Product: 50090-0423

NDC: 50090-0423-0 118 mL in a BOTTLE, PLASTIC